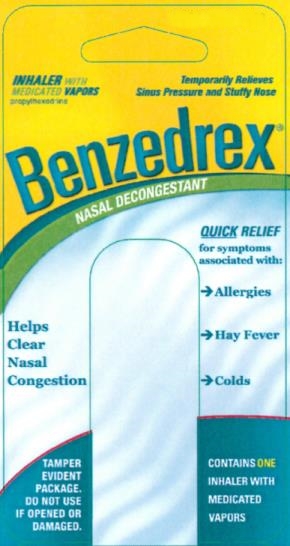 DRUG LABEL: BENZEDREX
NDC: 0225-0611 | Form: INHALANT
Manufacturer: BF ASCHER AND CO INC
Category: otc | Type: HUMAN OTC DRUG LABEL
Date: 20241205

ACTIVE INGREDIENTS: PROPYLHEXEDRINE 175 mg/1 1
INACTIVE INGREDIENTS: LAVENDER OIL; MENTHOL

Benzedrex

Active ingredient................. Purpose
Propylhexedrine 175 mg......Nasal decongestant

Uses

For the temporarily relief of nasal congestion due to a cold, hay fever, or other upper respiratory allergies (allergic rhinitis).

Uses
Temporarily relieves nasal congestion due to a cold, hay fever, or other upper respiratory allergies (allergic rhinitis).

Warnings

- Do not exceed recommended dosage.
- This product may cause temporary discomfort such as burning, stinging, sneezing, or an increase in nasal discharge.
- The use of this container by more than one person may spread infection.
- Use only as directed.
- Frequent or prolonged use may cause nasal congestion to recur or worsen.
- Ill effects may result if taken internally

DO NOT USE

Do not usethis product for more than three days.

Stop use and consult a doctorif symptoms persist.

PREGNANCY OR BREAST FEEDING

If pregnant or breast-feeding,ask a health professional before use.

KEEP OUT OF REACH OF CHILDREN

Keep this and all drugs out of reach of children.In case of overdose or ingestion of contents, get medical help or contact a poison control center immediately.

Directions

- adults and children 6 to 12 years of age (with adult supervision): two inhalations in each nostril not more than every two hours.
- children under 6 years of age: consult a doctor

Directions

- adults and children 6 to 12 years of age (with adult supervision): two inhalations in each nostril not more than every two hours.
- children under 6 years of age: consult a doctor

Other information

- store at 59°-86° F (15°-30° C)
- keep inhaler tightly closed
- mfd. in USA for B.F. Ascher & Co., Inc.
- this inhaler is effective for a minimum of 3 months after first use

Inactive ingredients

lavender oil, menthol

Questions?

Call 1-800-324-1880, 7:30am - 4:00pm Central, Mon. - Fri., or visit us at www.bfascher.com